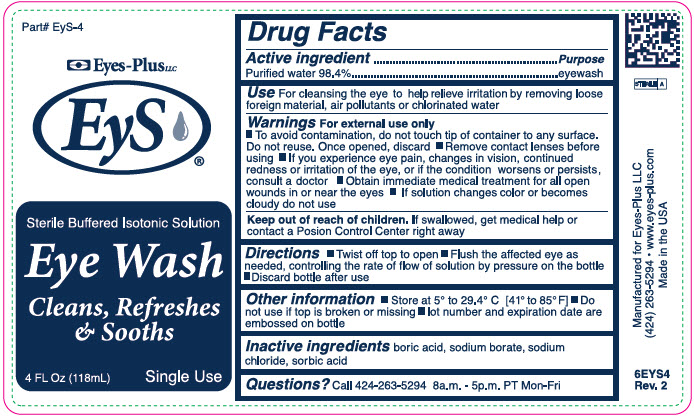 DRUG LABEL: EyS Eye Wash
NDC: 57349-220 | Form: SOLUTION
Manufacturer: Eyes-Plus LLC
Category: otc | Type: HUMAN OTC DRUG LABEL
Date: 20241015

ACTIVE INGREDIENTS: Water 14.85 mL/15 mL
INACTIVE INGREDIENTS: Boric Acid; Sodium Borate; Sodium Chloride; Sorbic Acid

EyS Eye Wash

Drug Facts

Active Ingredient

Purified Water USP 98.4%

Purpose

Eyewash

Use

For cleansing the eye to help relieve irritation by removing loose foreign material

Warnings

- To avoid contamination, do not touch tip of container to any surface. Do not reuse. Once opened, discard
- If you experience eye pain, changes in vision, continued redness or irritation of the eye, or if the condition worsens or persists, consult a doctor
- Obtain immediate medical treatment for all open wounds in or near the eyes If solution changes color or becomes cloudy do not use

KEEP OUT OF REACH OF CHILDREN

Directions

Flush the affected eye as needed, controlling the rate of flow of solution by pressure on the bottle

Other information

- Store at 41° to 85°F
- Do not use if top is broken or missing

Inactive ingredients

boric acid, sodium borate, sodium chloride, sorbic acid

PRINCIPAL DISPLAY PANEL - 118 mL Bottle Label

Part# EyS-4

Eyes-PlusLLC

EyS

Sterile Buffered Isotonic Solution
Eye Wash
Cleans, Refreshes
& Sooths

4 FL Oz (118mL)
Single Use